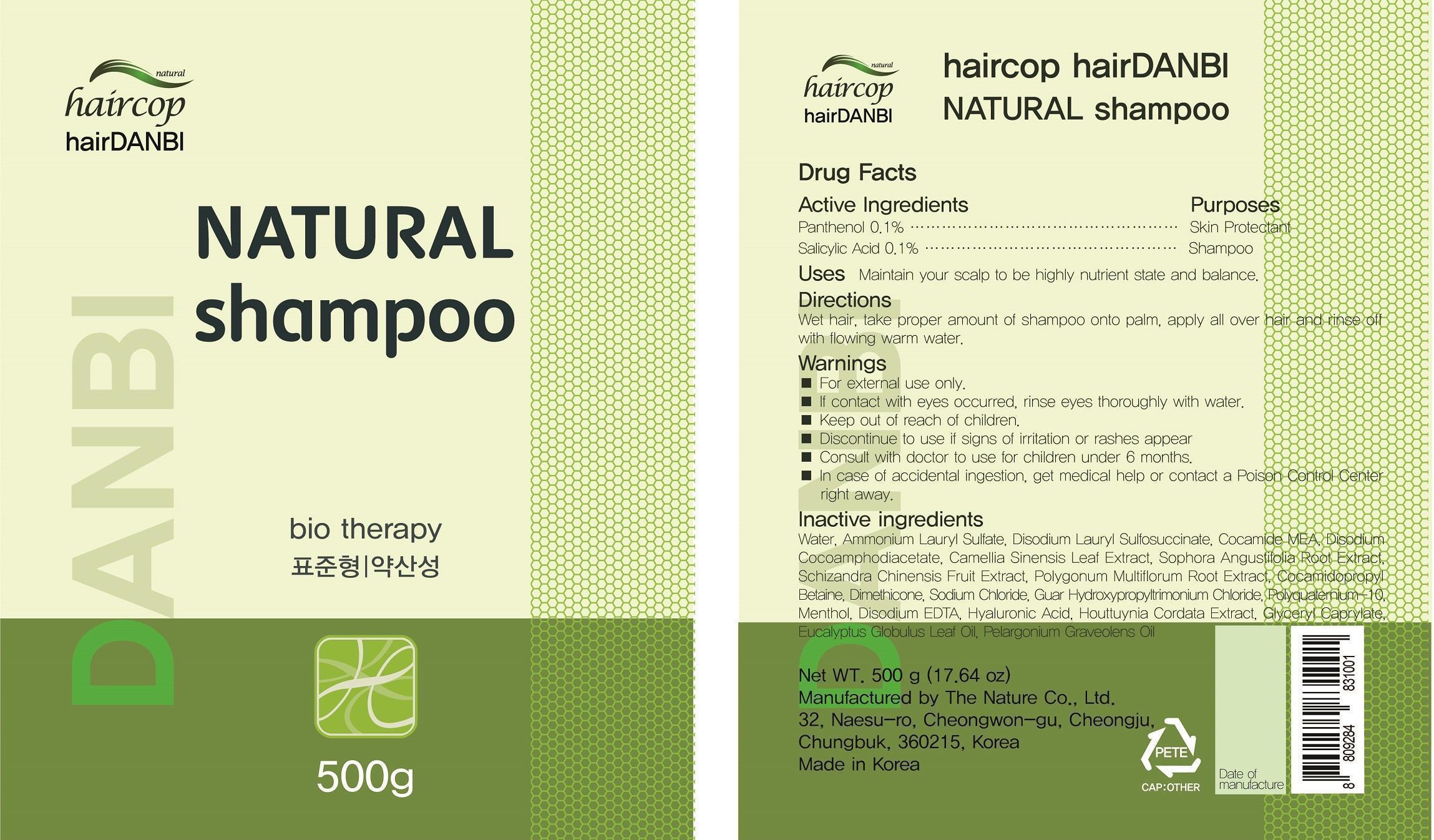 DRUG LABEL: haircop hairDANBI NATURAL
NDC: 69838-001 | Form: SHAMPOO
Manufacturer: The Nature Co., Ltd.
Category: otc | Type: HUMAN OTC DRUG LABEL
Date: 20150519

ACTIVE INGREDIENTS: PANTHENOL 0.5 g/500 g; SALICYLIC ACID 0.5 g/500 g
INACTIVE INGREDIENTS: WATER; AMMONIUM LAURYL SULFATE; DISODIUM LAURYL SULFOSUCCINATE; COCO MONOETHANOLAMIDE; DISODIUM COCOAMPHODIACETATE; GREEN TEA LEAF; SOPHORA FLAVESCENS ROOT; SCHISANDRA CHINENSIS FRUIT; FALLOPIA MULTIFLORA ROOT; COCAMIDOPROPYL BETAINE; DIMETHICONE; SODIUM CHLORIDE; GUAR HYDROXYPROPYLTRIMONIUM CHLORIDE (1.7 SUBSTITUENTS PER SACCHARIDE); POLYQUATERNIUM-10 (400 MPA.S AT 2%); MENTHOL, UNSPECIFIED FORM; EDETATE DISODIUM; HYALURONIC ACID; HOUTTUYNIA CORDATA FLOWERING TOP; EUCALYPTUS OIL; GERANIUM OIL, ALGERIAN TYPE

Drug Facts

ACTIVE INGREDIENT

PANTHENOL (0.01%)

SALICYLIC ACID (0.01%)

PURPOSE

Skin Protectant, shampoo

INDICATIONS AND USAGE

Maintain your scalp to be highly nutrient state and balance

DOSAGE AND ADMINISTRATION

Wet hair, take proper amount of shampoo onto palm, apply all over hair and rinse off with flowing warm water

WARNINGS

For external use only

If contact with eyes occured, rinse eyes thoroughly with water

Discontinue to use if signs of irritation or rashes appear

In case of accidental ingestion, get medical help or contact a poison control center right away

Keep out of reach of children

Consult with a doctor to use for children under 6 months

INACTIVE INGREDIENT

Water, Disodium Laureth Sulfosuccinate, Camellia Sinensis Leaf Extract, Ammonium Lauryl Sulfate, Cocamidopropyl Betaine, Sodium Chloride, Sophora Angustifolia Root Extract, Polygonum Multiflorum Root Extract, Dimethicone, Cocamide MEA, Guar Hydroxypropyltrimonium Chloride, Polyquaternium-10, Menthol, Disodium EDTA, Lecithin, Glyceryl Caprylate, Laureth-3, Laureth-20, Eucalyptus Globulus Leaf Oil, Camellia Japonica Seed Oil, Houttuynia Cordata Extract